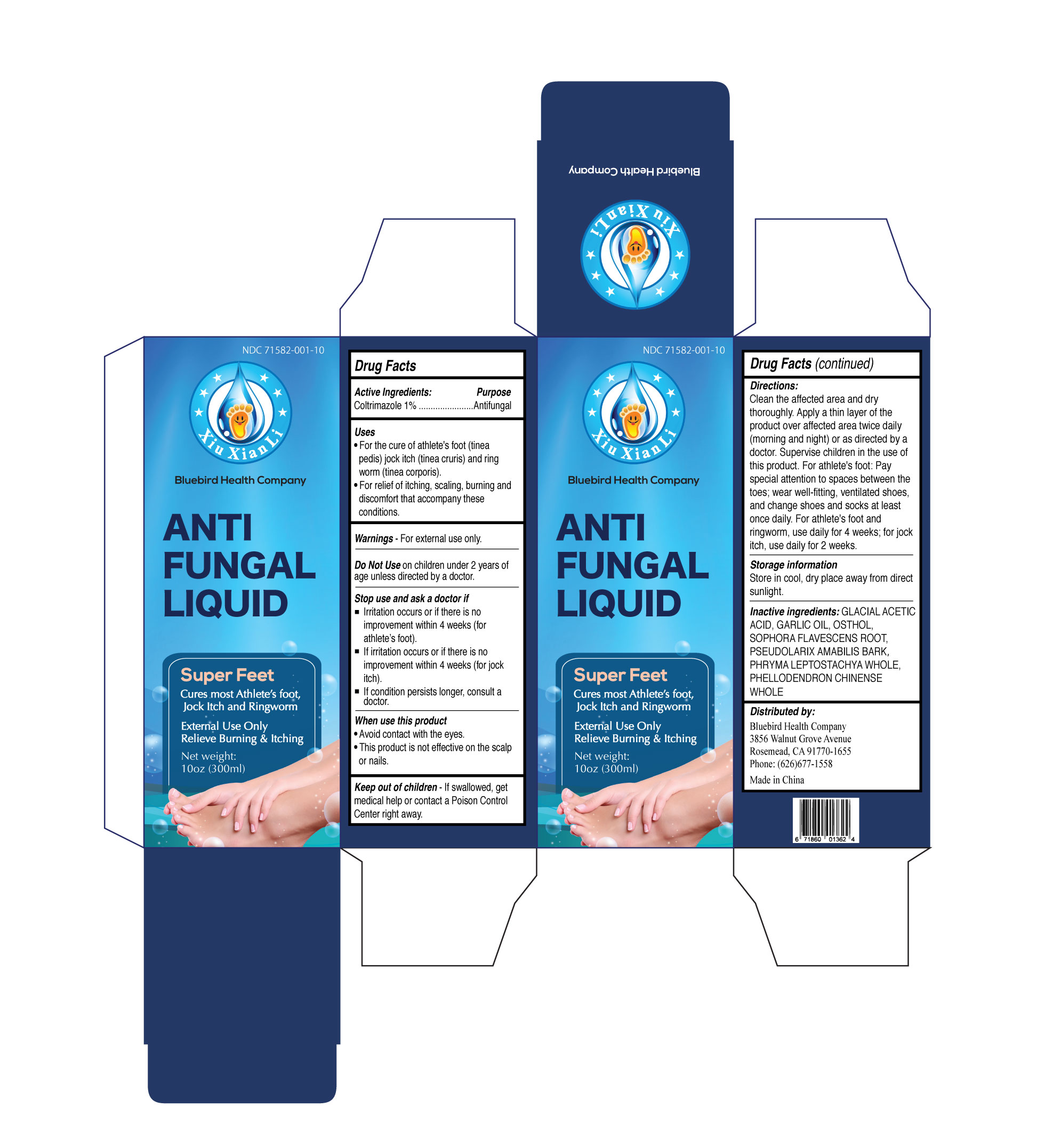 DRUG LABEL: Anti Fungal
NDC: 71582-001 | Form: LIQUID
Manufacturer: Guangzhou Ertiantang Pharmaceutical Co.,Ltd
Category: otc | Type: HUMAN OTC DRUG LABEL
Date: 20231215

ACTIVE INGREDIENTS: CLOTRIMAZOLE 1 g/100 mL
INACTIVE INGREDIENTS: ACETIC ACID; GARLIC OIL; OSTHOL; SOPHORA FLAVESCENS ROOT; PSEUDOLARIX AMABILIS BARK; PHRYMA LEPTOSTACHYA WHOLE; PHELLODENDRON CHINENSE WHOLE

Guangzhou Ertiantang Pharmaceutical Co.,Ltd

Active Ingredients

Clotrimazole 1%

Purpose

Coltrimazole 1% Antifungal

Uses

• For the cure of athlete's foot (tinea pedis), jock itch (tinea cruris) and ring worm (tinea corporis).
• For relief of itching, scaling, burning and discomfort that accompany these conditions.

Warnings

For External Use Only.

Do Not Use

On children under 2 years of age unless directed by a doctor.

Stop Use and Ask a Doctor if

• Irritation occurs or if there is no improvement within 4 weeks (for athlete’s foot).
• If irritation occurs or if there is no improvement within 4 weeks (for jock itch).
• If condition persists longer, consult a doctor.

When Use This Product

• Avoid contact with the eyes.
• This product is not effective on the scalp or nails.

Keep Out of Reach of Children

If swallowed, get medical help or contact a Poison Control Center right away.

Directions

Clean the affected area and dry thoroughly. Apply a thin layer of the product over affected area twice daily (morning and night) or as directed by a doctor. Supervise children in the use of this product. For athlete's foot: Pay special attention to spaces between the toes; wear well-fitting, ventilated shoes, and change shoes and socks at least once daily. For athlete's foot and ringworm, use daily for 4 weeks; for jock itch, use daily for 2 weeks.

Storage

Store in cool, dry place away from direct sunlight.

Inactive Ingredients

GLACIAL ACETIC ACID, GARLIC OIL, OSTHOL, SOPHORA FLAVESCENS ROOT, PSEUDOLARIX AMABILIS BARK，PHRYMA LEPTOSTACHYA WHOLE, PHELLODENDRON CHINENSE WHOLE

Distributed by:

Bluebird Health Company
3856 Walnut Grove Avenue
Rosemead, CA 91770-1655
Phone: (626)677-1558

Made in China